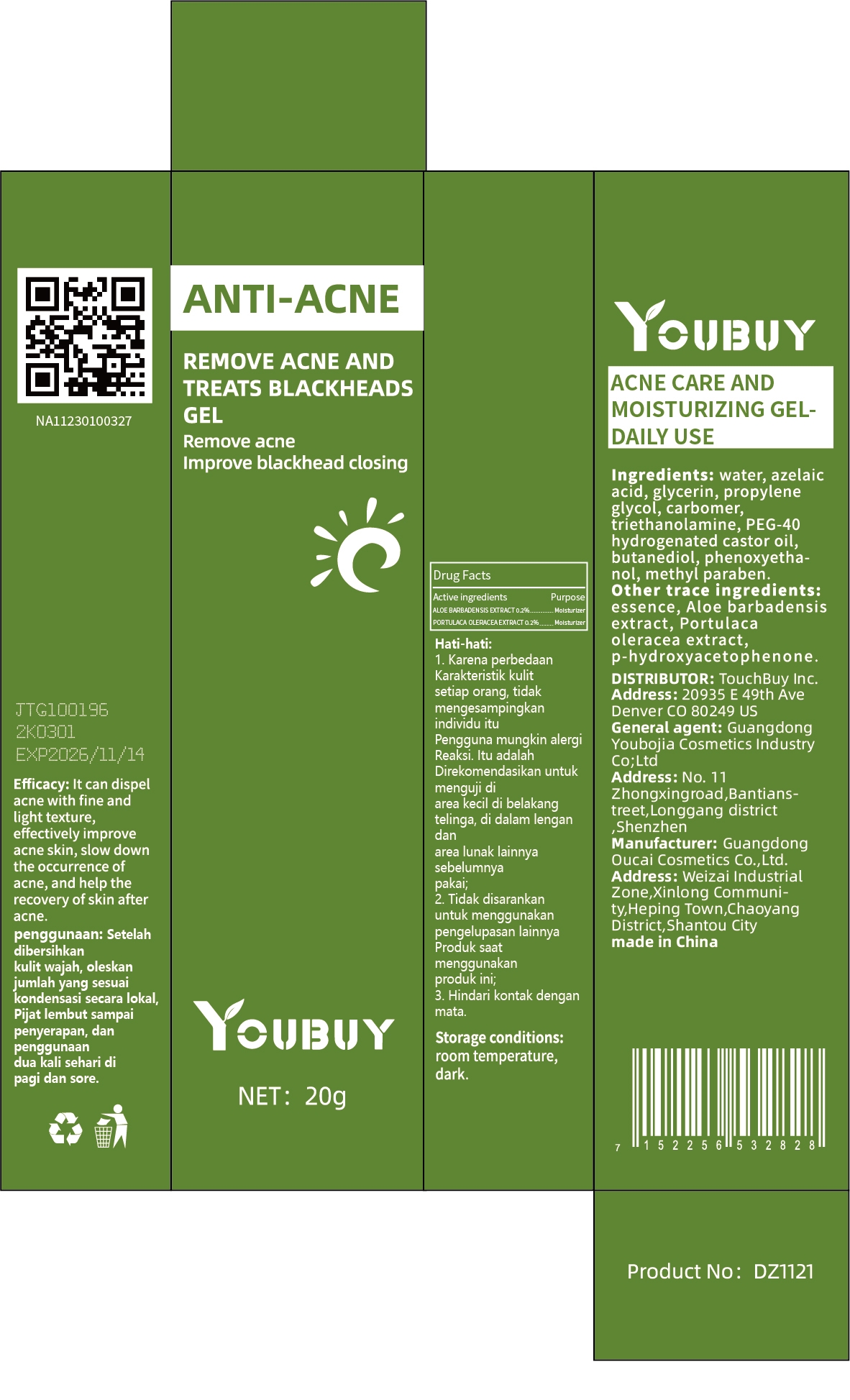 DRUG LABEL: YOUBUY Acne Care and Moisturizing Gel-Daily Use
NDC: 84712-043 | Form: GEL
Manufacturer: Guangdong Youbaijia Cosmetic Industry Co., Ltd
Category: otc | Type: HUMAN OTC DRUG LABEL
Date: 20241128

ACTIVE INGREDIENTS: PORTULACA OLERACEA LEAF 0.04 g/20 g; ALOE BARBADENSIS LEAF 0.04 g/20 g
INACTIVE INGREDIENTS: GLYCERIN 1 g/20 g

ACTIVE INGREDIENT

ALOE BARBADENSIS EXTRACT 0.2%
PORTULACA OLERACEA EXTRACT 0.2%

INACTIVE INGREDIENT

water, azelaic acid, glycerin, propylene glycol, carbomer,triethanolamine, PEG-40 hydrogenated castor oil,butanediol, phenoxyethanol, methyl paraben. essence,p-hydroxyacetophenone.

Do not use on damaged or broken skin

Keep away from children. Do not swallow.

PURPOSE

dispel acne

QUESTIONS

Contact name: Jessie Peng
Company phone number: +1 818 579 7288
Company e-mail: jessie@registeragentllc.com

STOP USE

lf skin becomes red or irritated, discontinue use immediately and wash with water.

WHEN USING

keep out of eyes. Rinse with water to remove.

WARNINGS

For external use only.

INDICATIONS AND USAGE

lt can dispel acne with fine and light texture,effectively improve acne skin, slow down the occurrence of acne, and help the recovery of skin after acne.

DOSAGE AND ADMINISTRATION

After facial cleaning, adjust the local condensation amount, mild to absorption, and twice daily in the morning and evening.

STORAGE AND HANDLING

Keep away from light and in a dry place.